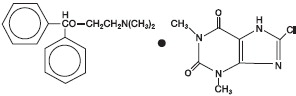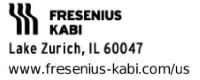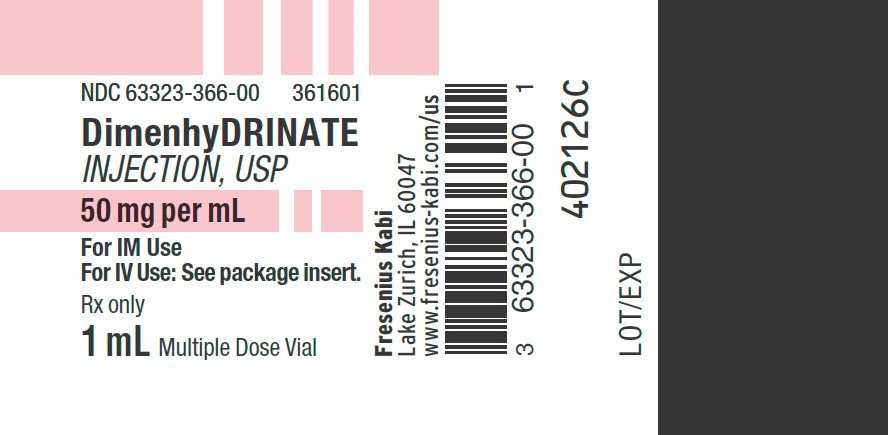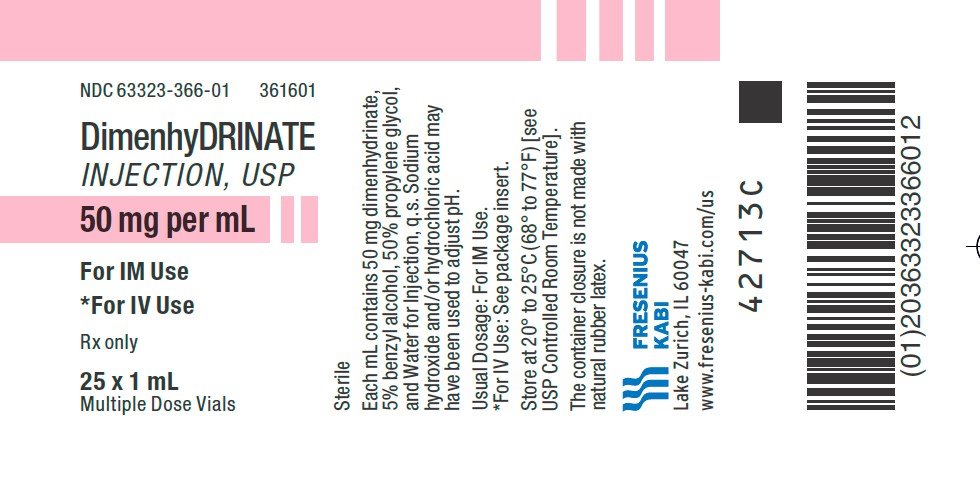 DRUG LABEL: Dimenhydrinate
NDC: 63323-366 | Form: INJECTION, SOLUTION
Manufacturer: Fresenius Kabi USA, LLC
Category: prescription | Type: HUMAN PRESCRIPTION DRUG LABEL
Date: 20250115

ACTIVE INGREDIENTS: DIMENHYDRINATE 50 mg/1 mL
INACTIVE INGREDIENTS: BENZYL ALCOHOL 0.05 mL/1 mL; PROPYLENE GLYCOL 0.5 mL/1 mL; SODIUM HYDROXIDE; HYDROCHLORIC ACID; WATER

Dimenhydrinate Injection USP

Rx only

DESCRIPTION

Dimenhydrinate, an anti-nauseant/antiemetic, is the 8-chlorotheophylline salt of diphenhydramine. It contains not less than 53% and not more than 55.5% of diphenhydramine, and not less than 44% and not more than 47% of 8-chlorotheophylline, calculated on the dried basis. Chemically, it is 8-chlorotheophylline compound with 2(diphenylmethoxy)-N,N-dimethylethylamine (1:1), and the structural formula is:

C17H21NO•C7H7ClN4O2 M.W. 469.96

Dimenhydrinate Injection, USP contains a sterile solution of Dimenhydrinate 50 mg/mL; Propylene Glycol 50%; Benzyl Alcohol 5% as preservative; and Water for Injection q.s. Sodium Hydroxide and/or Hydrochloric Acid may have been used to adjust pH.

CLINICAL PHARMACOLOGY

While the precise mode of action of dimenhydrinate is not known, it has a depressant action on hyperstimulated labyrinthine function.

INDICATIONS AND USAGE

Dimenhydrinate Injection, USP is indicated for the prevention and treatment of nausea, vomiting, or vertigo of motion sickness.

CONTRAINDICATIONS

Neonates and patients with a history of hypersensitivity to dimenhydrinate or its components (diphenhydramine or 8-chlorotheophylline) should not be treated with dimenhydrinate.

Note: This product contains Benzyl Alcohol. Benzyl Alcohol has been associated with a fatal “Gasping Syndrome” in premature infants and infants of low birth weight.

WARNINGS

Caution should be used when dimenhydrinate is given in conjunction with certain antibiotics that may cause ototoxicity, since dimenhydrinate is capable of masking ototoxic symptoms, and an irreversible state may be reached.

This drug may impair the mental and/or physical abilities required for the performance of potentially hazardous tasks, such as driving a vehicle or operating machinery. The concomitant use of alcohol or other central nervous system depressants may have an additive effect. Therefore, patients should be warned accordingly.

Dimenhydrinate should be used with caution in patients having conditions which might be aggravated by anticholinergic therapy (i.e., prostatic hypertrophy, stenosing peptic ulcer, pyloroduodenal obstruction, bladder neck obstruction, narrow-angle glaucoma, bronchial asthma, or cardiac arrhythmias).

The preparation should not be injected intra-arterially.

Pediatric Patients

For infants and children especially, antihistamines in overdosage may cause hallucinations, convulsions, or death.

As in adults, antihistamines may diminish mental alertness in pediatric patients. In the young child, particularly, they may produce excitation (see CONTRAINDICATIONS).

PRECAUTIONS

General

Drowsiness may be experienced by some patients, especially with high dosage. This effect frequently is not undesirable in conditions for which the drug is used.

Information for Patients

Because of the potential for drowsiness, patients taking dimenhydrinate should be cautioned against operating automobiles or dangerous machinery (see WARNINGS).

Carcinogenesis, Mutagenesis, Impairment of Fertility

Mutagenicity screening tests performed with dimenhydrinate, diphenhydramine, and 8-chlorotheophylline produced positive results in the bacterial systems and negative results in the mammalian systems. There are no human data that indicate dimenhydrinate is a carcinogen or mutagen or that it impairs fertility.

Pregnancy

Pregnancy Category B.

Reproduction studies have been performed in rats at doses up to 20 times the human dose, and in rabbits at doses up to 25 times the human dose (on a mg/kg basis), and have revealed no evidence of impaired fertility or harm to the fetus due to dimenhydrinate. There are no adequate and well-controlled studies in pregnant women. However, clinical studies in pregnant women have not indicated that dimenhydrinate increases the risk of abnormalities when administered in any trimester of pregnancy. It would appear that the possibility of fetal harm is remote when the drug is used during pregnancy. Nevertheless, because the studies in humans cannot rule out the possibility of harm, dimenhydrinate should be used during pregnancy only if clearly needed.

Labor and Delivery

The safety of dimenhydrinate given during labor and delivery has not been established. Reports have indicated dimenhydrinate may have an oxytocic effect. Caution is advised when this effect is unwanted or in situations where it may prove detrimental.

Nursing Mothers

Small amounts of dimenhydrinate are excreted in breast milk. Because of the potential for adverse reactions in nursing infants from dimenhydrinate, a decision should be made whether to discontinue nursing or to discontinue the drug, taking into account the importance of the drug to the mother.

ADVERSE REACTIONS To report SUSPECTED ADVERSE REACTIONS, contact Fresenius Kabi USA, LLC at 1-800-551-7176 or FDA at 1-800-FDA-1088 or www.fda.gov/medwatch.

The most frequent adverse reaction to dimenhydrinate is drowsiness. Dizziness may also occur. Symptoms of dry mouth, nose and throat, blurred vision, difficult or painful urination, headache, anorexia, nervousness, restlessness or insomnia (especially in pediatric patients), skin rash, thickening of bronchial secretions, tachycardia, epigastric distress, lassitude, excitation, and nausea have been reported.

OVERDOSAGE

Drowsiness is the usual clinical side effect. Convulsions, coma, and respiratory depression may occur with massive overdosage. No specific antidote is known. If respiratory depression occurs, mechanically assisted respiration should be initiated and oxygen should be administered. Convulsions should be treated with appropriate doses of diazepam. Phenobarbital (5 to 6 mg/kg) may be given to control convulsions in pediatric patients.

The oral LD50 in mice and rats is 203 mg/kg and 1320 mg/kg, respectively. The intraperitoneal LD50 in mice is 149 mg/kg.

DOSAGE AND ADMINISTRATION

Dimenhydrinate in the injectable form is indicated when the oral form is impractical.

Adults

Nausea or vomiting may be expected to be controlled for approximately 4 hours with 50 mg, and prevented by a similar dose every 4 hours. Its administration may be attended by some degree of drowsiness in some patients, and 100 mg every 4 hours may be given in conditions in which drowsiness is not objectionable or is even desirable.

For intramuscular administration, each milliliter (50 mg) of solution is injected as needed, but for intravenous administration, each milliliter (50 mg) of solution must be diluted in 10 mL of 0.9% Sodium Chloride Injection, USP and injected over a period of 2 minutes.

Pediatric

For intramuscular administration, 1.25 mg/kg of body weight or 37.5 mg/m^2 of body surface area is administered four times daily. The maximum dose should not exceed 300 mg daily (see CONTRAINDICATIONS).

Parenteral drug products should be inspected visually for particulate matter and discoloration prior to administration, whenever solution and container permit.

HOW SUPPLIED

DimenhyDRINATE Injection, USP, 50 mg/mL is available in multiple dose amber vials, as follows:

Product Code | Unit of Sale | Strength | Each
361601 | NDC 63323-366-01 Unit of 25 | 50 mg per mL | NDC 63323-366-00 1 mL in a 2 mL multiple dose vial

Protect from light.

Store at 20° to 25°C (68° to 77°F) [see USP Controlled Room Temperature].

The container closure is not made with natural rubber latex.

45981C

Revised: August 2024

PACKAGE LABEL

PACKAGE LABEL - PRINCIPAL DISPLAY - Dimenhydrinate 1 mL Vial Label

NDC 63323-366-00 361601

DimenhyDRINATE
INJECTION, USP

50 mg per mL

For IM Use
For IV Use: See package insert.

Rx only

1 mL Multiple Dose Vial

PACKAGE LABEL - PRINCIPAL DISPLAY - Dimenhydrinate 1 mL Vial Tray Label

NDC 63323-366-01 361601

DimenhyDRINATE
INJECTION, USP

50 mg per mL

For IM Use

*For IV Use

Rx only

25 x 1 mL
Multiple Dose Vials